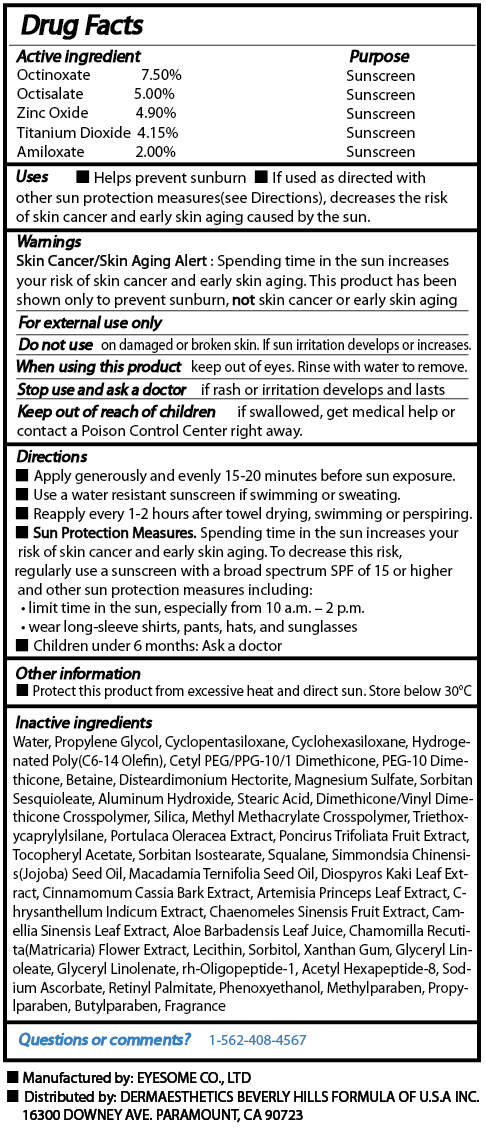 DRUG LABEL: EGF UV SHIELD
NDC: 58831-1001 | Form: CREAM
Manufacturer: Dermaesthetics Inc.
Category: otc | Type: HUMAN OTC DRUG LABEL
Date: 20191222

ACTIVE INGREDIENTS: OCTINOXATE 7.5 g/60 g; OCTISALATE 5 g/60 g; ZINC OXIDE 4.9 g/60 g; TITANIUM DIOXIDE 4.15 g/60 g; AMILOXATE 2 g/60 g
INACTIVE INGREDIENTS: WATER; PROPYLENE GLYCOL; CYCLOMETHICONE 5; CYCLOMETHICONE 6; CETYL PEG/PPG-10/1 DIMETHICONE (HLB 3); PEG-10 DIMETHICONE (600 CST); BETAINE; DISTEARDIMONIUM HECTORITE; MAGNESIUM SULFATE, UNSPECIFIED; SORBITAN SESQUIOLEATE; ALUMINUM HYDROXIDE; STEARIC ACID; DIMETHICONE/VINYL DIMETHICONE CROSSPOLYMER (SOFT PARTICLE); SILICON DIOXIDE; TRIETHOXYCAPRYLYLSILANE; PURSLANE; PONCIRUS TRIFOLIATA FRUIT; .ALPHA.-TOCOPHEROL ACETATE; SORBITAN ISOSTEARATE; SQUALANE; JOJOBA OIL; MACADAMIA OIL; DIOSPYROS KAKI LEAF; CHINESE CINNAMON; ARTEMISIA PRINCEPS LEAF; CHRYSANTHELLUM INDICUM TOP; CHAENOMELES SINENSIS FRUIT; GREEN TEA LEAF; ALOE VERA LEAF; CHAMOMILE; EGG PHOSPHOLIPIDS; SORBITOL; XANTHAN GUM; GLYCERYL MONOLINOLEATE; GLYCERYL LINOLENATE; ACETYL HEXAPEPTIDE-8; SODIUM ASCORBATE; VITAMIN A PALMITATE; PHENOXYETHANOL; METHYLPARABEN; PROPYLPARABEN; BUTYLPARABEN

EGF UV Shield

Drug Fact

Active ingredient
Octinoxate 7.50%
Octisalate 5.00%
Zinc Oxide 4.90%
Titanium Dioxide 4.15%
Amiloxate 2.00%

Purpose

Sunscreen

Keep out of reach of children

Stop use and ask a doctor
if rash or irritation develops and lasts.

Keep out of reach of children
if swallowed, get medical help or contact a Poison Control Center right away.

Indication & usage

Directions
Apply generously and evenly 15-20 minutes before sun exposure.

Use a water resistant sunscreen if swimming or sweating.

Reapply every 1-2 hours after towel drying, swimming or perspiring.

Sun Protection Measures.

Spending time in the sun increases your risk of skin cancer and early skin aging.

To decrease this risk, regularly use a sunscreen with a broad spectrum SPF of 15 or higher and other sun protection measures

including:

- limit time in the sun, especially from 10 a.m. ~ 2 p.m.

- wear long-sleeve shirts, pants, hats, and sunglasses

Children under 6 months: Ask a doctor

Warning

Warnings

Skin Cancer/Skin Aging Alert:

Spending time in the sun increases your risk of skin cancer and early skin aging.

This product has been shown only to prevent sunburn, not skin cancer or early skin aging.

For external use only.

Do not use on damaged or broken skin. If sun irritation develops or increases.

When using this product keep out of eyes. Rinse with water to remove.

Dosage & administration

Uses

Helps prevent sunburn.

If used as directed with other sun protection measures(see Directions),

decreases the risk of skin cancer and early skin aging caused by the sun.

Inactive ingredient

Water, Propylene Glycol, Cyclopentasiloxane, Cyclohexasiloxane, Hydrogenated Poly(C6-14 Olefin), Cetyl PEG/PPG-10/1 Dimethicone, PEG-10 Dimethicone, Betaine, Disteardimonium Hectorite, Magnesium Sulfate, Sorbitan Sesquioleate, Aluminum Hydroxide, Stearic Acid, Dimethicone/Vinyl Dimethicone Crosspolymer, Silica, Methyl Methacrylate Crosspolymer, Triethoxycaprylylsilane, Portulaca Oleracea Extract, Poncirus Trifoliata Fruit Extract, Tocopheryl Acetate, Sorbitan Isostearate, Squalane, Simmondsia Chinensis(Jojoba) Seed Oil, Macadamia Ternifolia Seed Oil, Diospyros Kaki Leaf Extract, Cinnamomum Cassia Bark Extract, Artemisia Princeps Leaf Extract, Chrysanthellum Indicum Extract, Chaenomeles Sinensis Fruit Extract, Camellia Sinensis Leaf Extract, Aloe Barbadensis Leaf Juice, Chamomilla Recutita(Matricaria) Flower Extract, Lecithin, Sorbitol, Xanthan Gum, Glyceryl Linoleate, Glyceryl Linolenate, rh-Oligopeptide-1, Acetyl Hexapeptide-8, Sodium Ascorbate, Retinyl Palmitate, Phenoxyethanol, Methylparaben, Propylparaben, Butylparaben, Fragrance

EGF UV Shield

Net WT. 2.03 fl. oz(60ml)